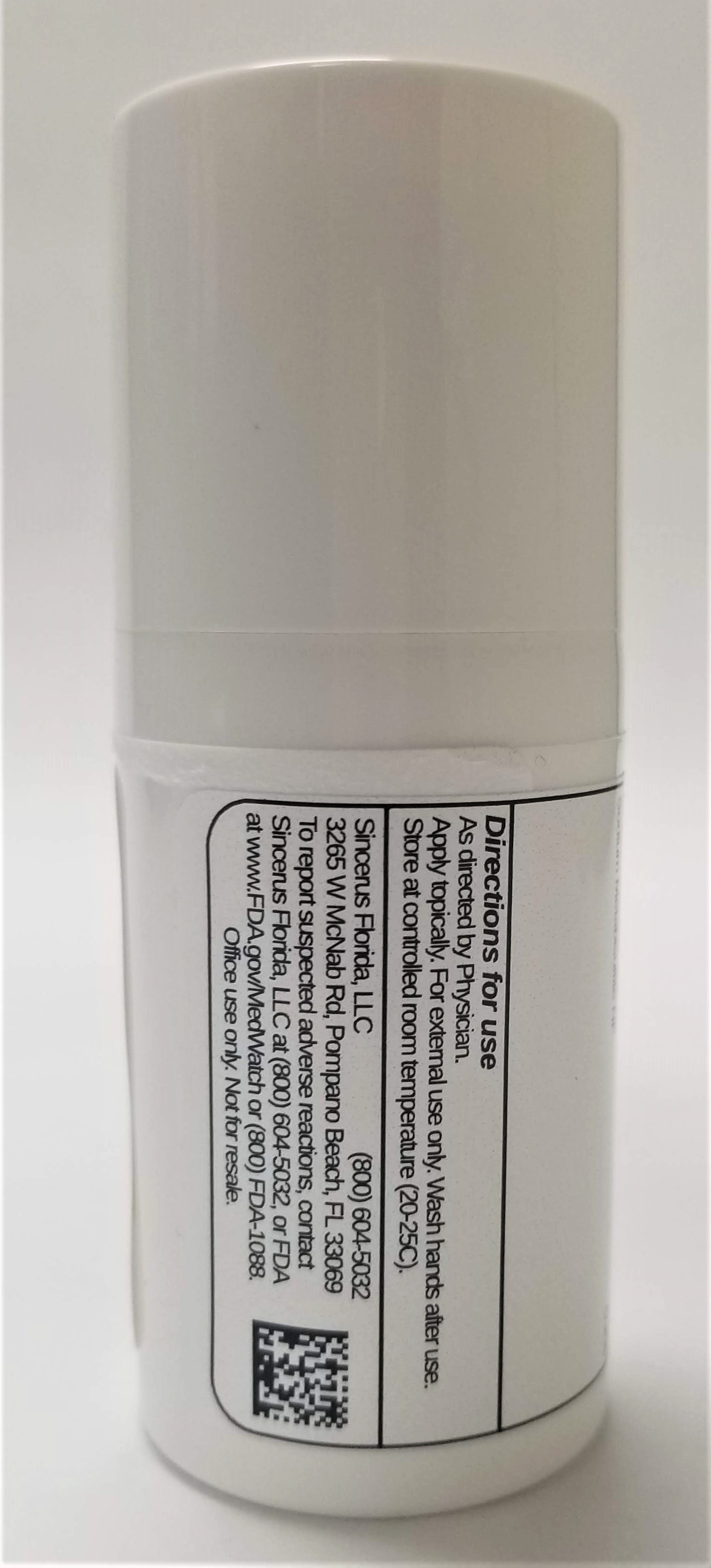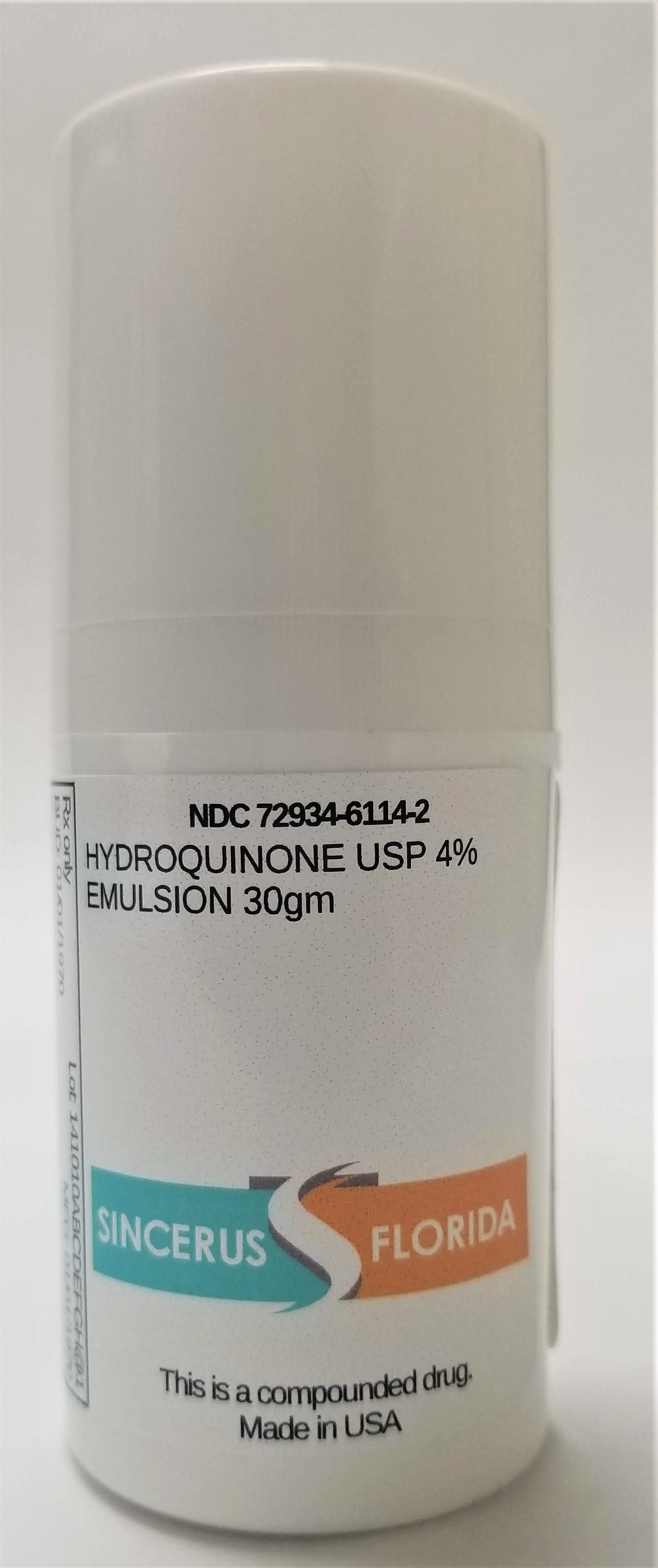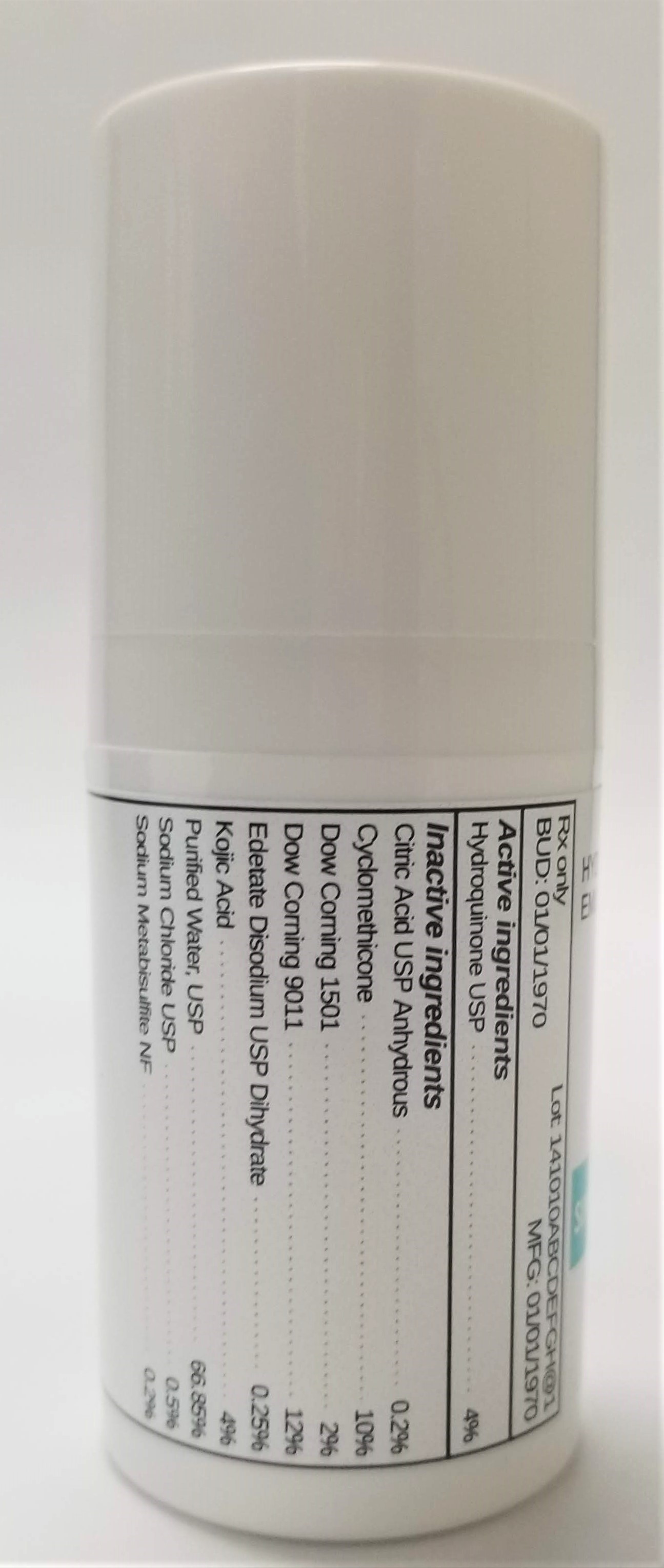 DRUG LABEL: HYDROQUINONE 4%
NDC: 72934-6114 | Form: EMULSION
Manufacturer: Sincerus Florida, LLC
Category: prescription | Type: HUMAN PRESCRIPTION DRUG LABEL
Date: 20190424

ACTIVE INGREDIENTS: HYDROQUINONE 4 g/100 g

HYDROQUINONE 4%